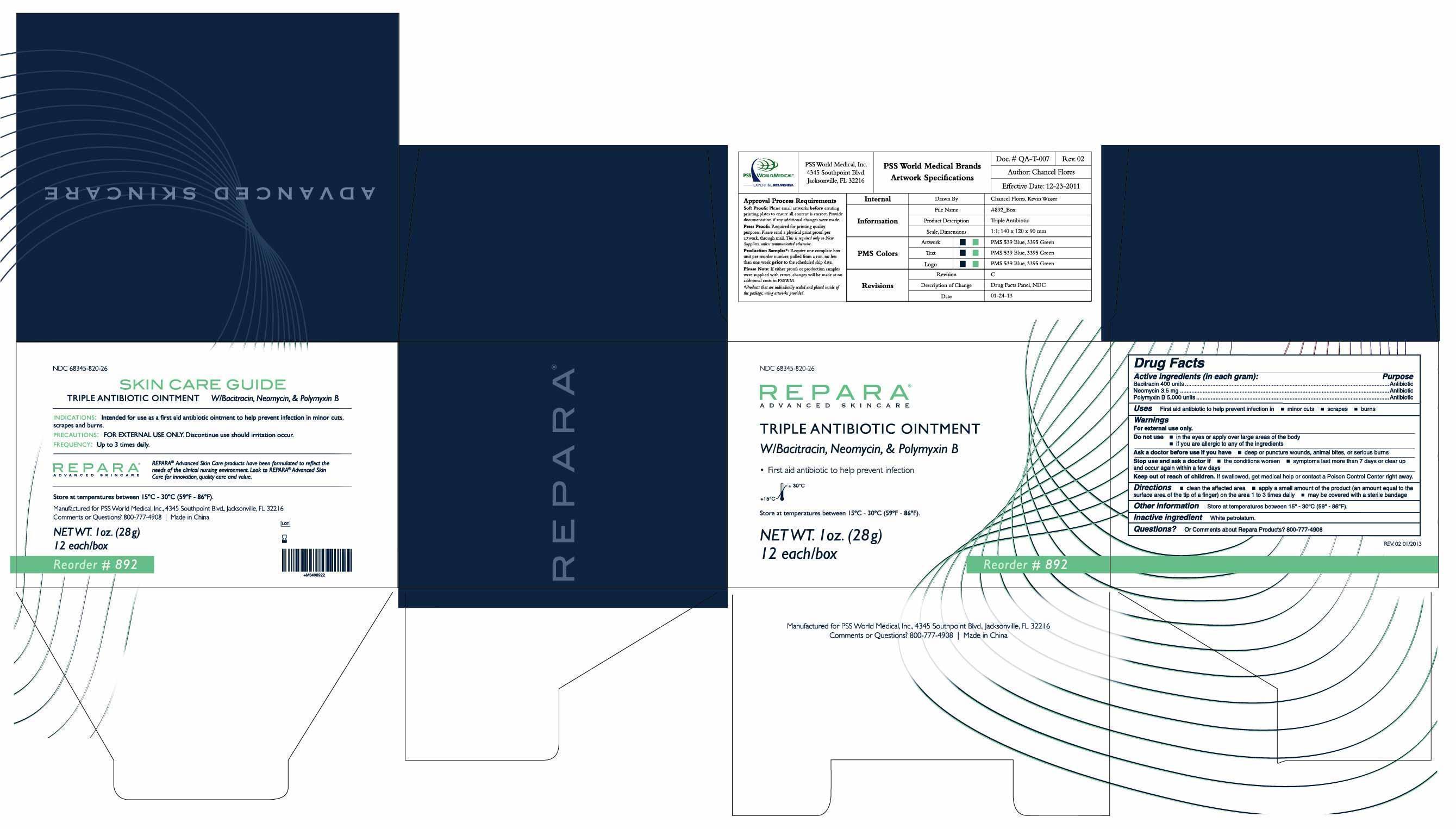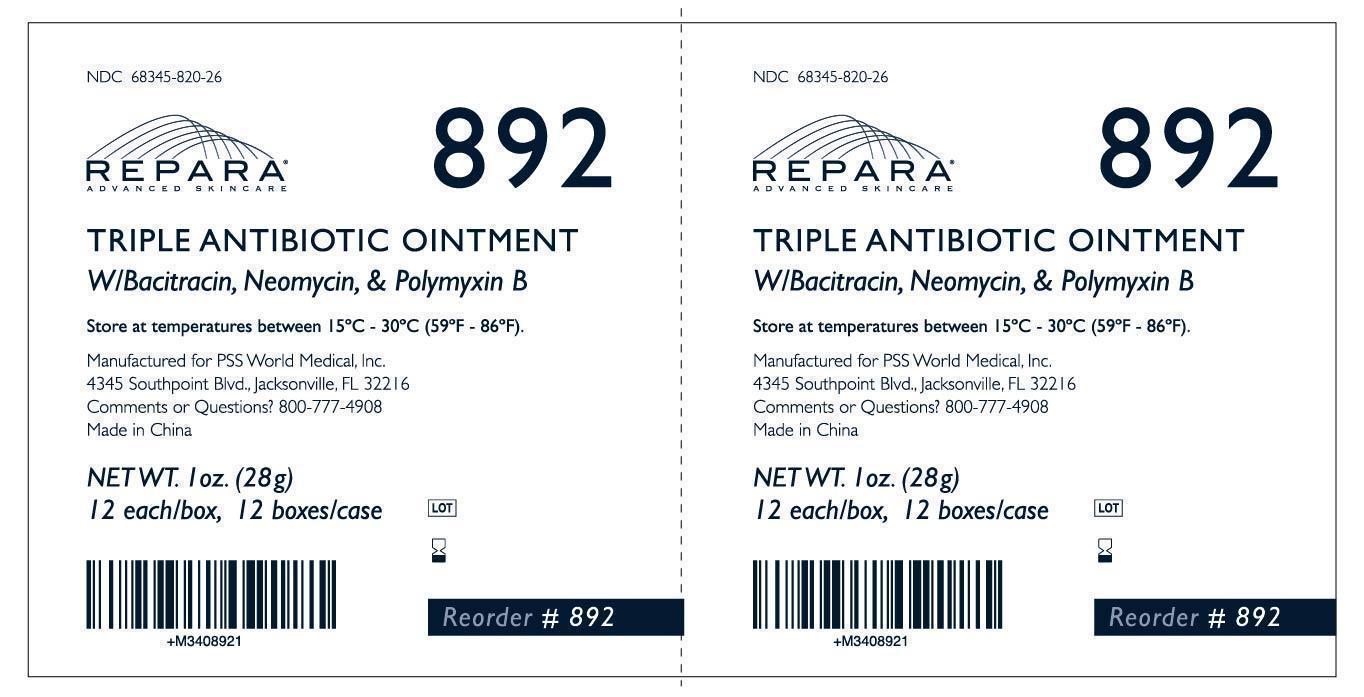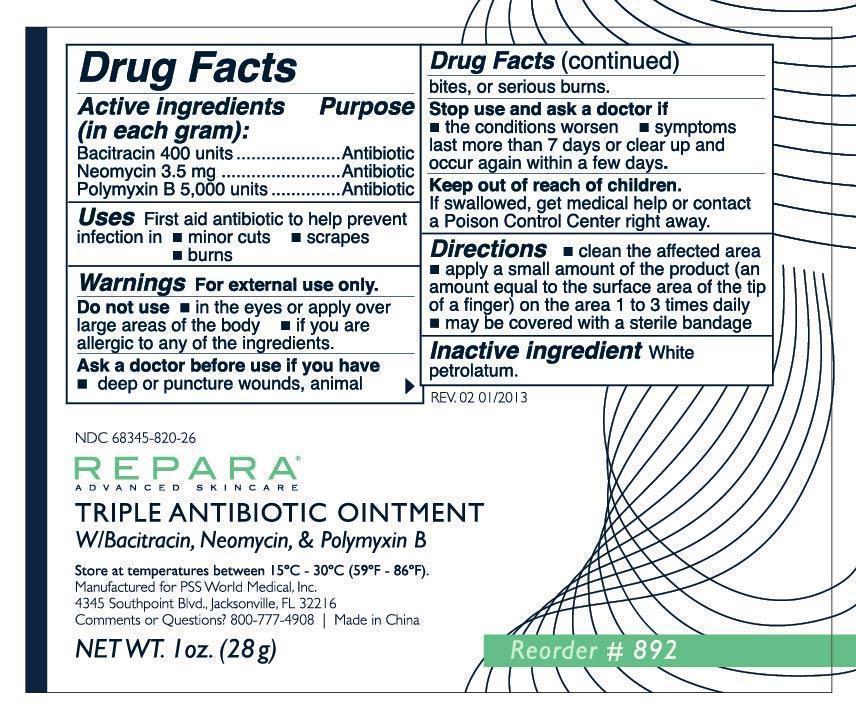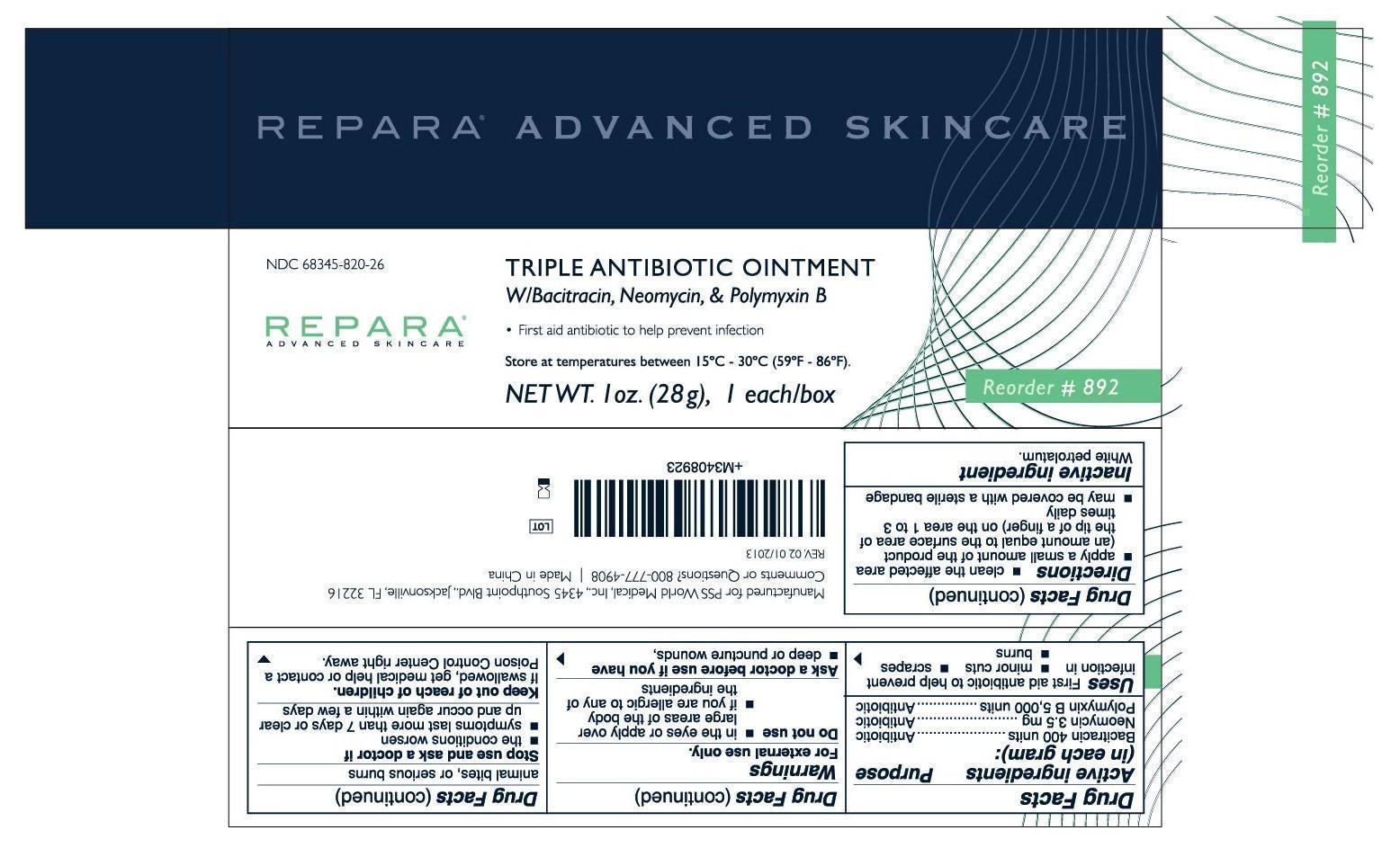 DRUG LABEL: Repara Triple Antibiotic
NDC: 68345-820 | Form: OINTMENT
Manufacturer: PSS WORLD MEDICAL, INC.
Category: otc | Type: HUMAN OTC DRUG LABEL
Date: 20130619

ACTIVE INGREDIENTS: BACITRACIN 400 [iU]/1 g; NEOMYCIN SULFATE 3.5 mg/1 g; POLYMYXIN B SULFATE 5000 [iU]/1 g
INACTIVE INGREDIENTS: PETROLATUM

REPARA (Triple Antibiotic), ointment

Active Igredients:

Bacitracin 400 units

Neomycin 3.5 mg

Polymyxin B 5,000 units

Purpose:

Antibiotic

Inactive Ingredients:

White petrolatum

KEEP OUT OF REACH OF CHILDREN

If swallowed, get medical help or contact a Poison Control Center right away.

Uses:

First aid antibiotic to help prevent infection in

- minor cuts
- scrapes
- burns

Warnings:

FOR EXTERNAL USE ONLY.

Do not use

• in the eyes or apply over large areas of the body

• if you are allergic to any of the ingredients

Ask a doctor before use if you have

• deep or puncture wounds, animal bites or serious burns

Stop use and ask a doctor if

• the condition worsen

• symptons last more than 7 days or clear up and occur again within a few days

Directions:

- clean the affected area
- apply a small amount of the product (an amount equal to the surface area of the tip of a finger) on the area 1 to 3 times daily
- may be covered with a sterile bandage

Comments or Questions?

800-777-4908

Manufactured for PSS World Medical, Inc.
4345 Southpoint Blvd., Jacksonville, FL 32216
Made in China

Storage Information

Store at temperature between 15°C - 30°C (59°F- 86°F).

Package Label

Repara® Advanced Skincare

NDC 68345-820-26

Triple Antibiotic Ointment Bacitracin•Neomycin•Polymyxin B

NET WT. 28g. Reorder #892

892_Each

892_EachBox

892_Box

892_Case